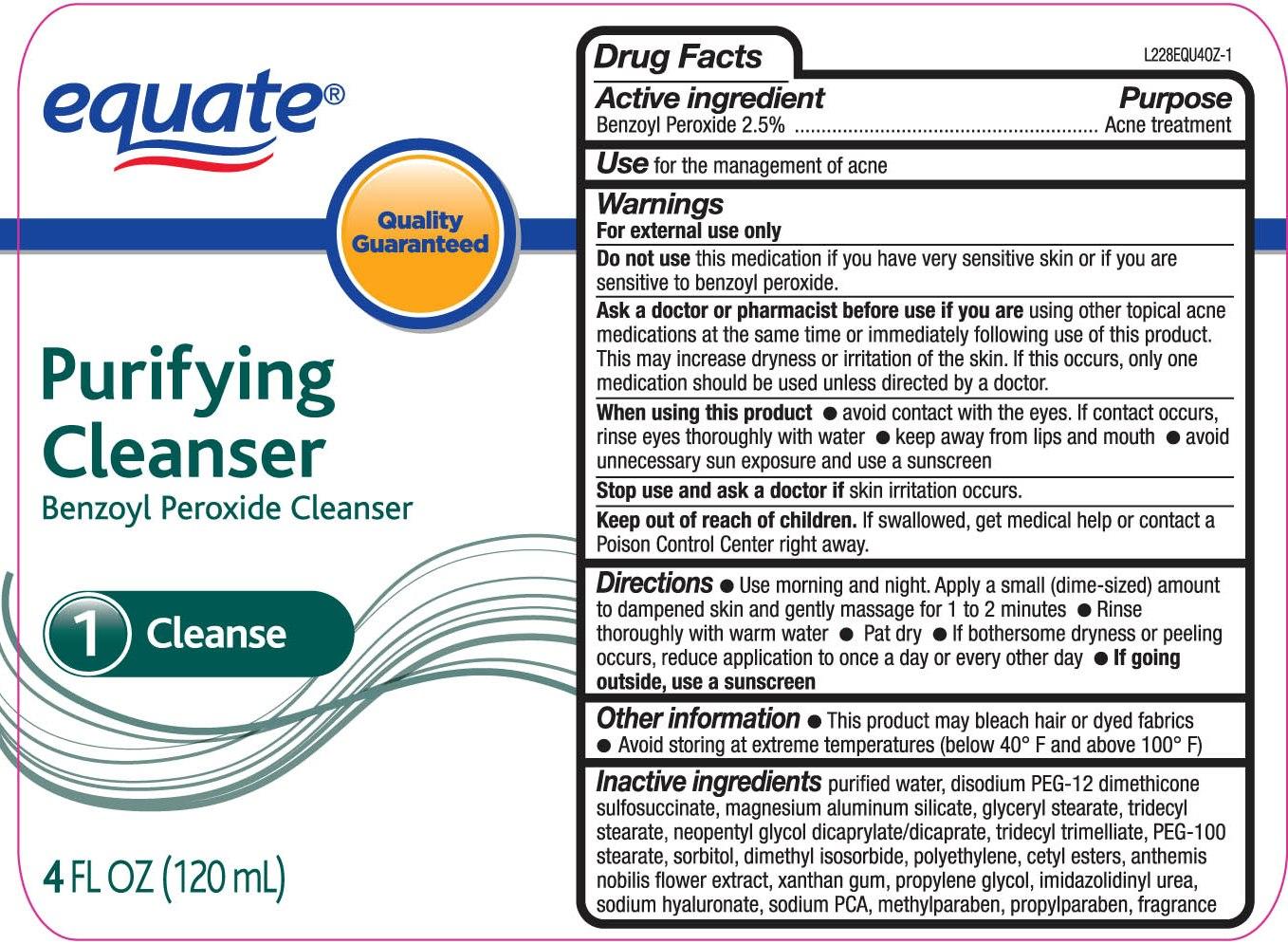 DRUG LABEL: Equate Purifying Cleanser
NDC: 49035-025 | Form: GEL
Manufacturer: Wal-Mart Stores Inc
Category: otc | Type: HUMAN OTC DRUG LABEL
Date: 20120426

ACTIVE INGREDIENTS: BENZOYL PEROXIDE 25 mg/1 mL
INACTIVE INGREDIENTS: WATER; MAGNESIUM ALUMINUM SILICATE; GLYCERYL MONOSTEARATE; PEG-100 STEARATE; PEG-12 DIMETHICONE (300 CST); SORBITOL; DIMETHYL ISOSORBIDE; TRIDECYL STEARATE; NEOPENTYL GLYCOL DICAPRYLATE/DICAPRATE; LOW DENSITY POLYETHYLENE; CETYL ESTERS WAX; CHAMOMILE; HYALURONATE SODIUM; SODIUM PYRROLIDONE CARBOXYLATE; XANTHAN GUM; IMIDUREA; METHYLPARABEN; PROPYLPARABEN

drug facts

Active ingredient Purpose
Benzoyl Peroxide, 2.5%.......................................Acne Treatment

PURPOSE

Use - for the management of acne

Keep out of reach of children.If swallowed, get medical help or contact a Poison
Control Center right away.

Directions

- Use morning and night. Apply a small (dime sized) amount to dampened skin and
gently massage for one to two minutes. - rinse thoroughly with warm water - pat dry
- if bothersome drying or peeling occurs, reduce application to once a day or every other day
- if going outside, use a sunscreen
Other Information
- this product may bleach hair or dyed fabrics
- avoid storing at extreme temperatures (below 40 degrees F and above 100 degrees F)

Warnings
For external use only.
Do not use this medication if you have very sensitive skin or if you are sensitive to benzoyl peroxide.
Ask a doctor or pharmacist before use if you are using other topical acne medications at the same time or immediately following the use of this product.
This may increase dryness or irritation of the skin. If this occurs, only one medication should be used unless directed by a doctor.
When using this product
- avoid contact with the eyes. If contact occurs, rinse eyes thoroughly with water
- Keep away from lips and mouth
- Avoid unnecessary sun exposure and use a sunscreen
Stop use and ask a doctor if skin irritation occurs.
Keep out of reach of children. If swallowed, get medical help or contact a Poison Control Center right away.

Directions

- Use morning and night. Apply a small (dime sized) amount to dampened skin and
gently massage for one to two minutes. - rinse thoroughly with warm water - pat dry
- if bothersome drying or peeling occurs, reduce application to once a day or every other day
- if going outside, use a sunscreen
Other Information
- this product may bleach hair or dyed fabrics
- avoid storing at extreme temperatures (below 40 degrees F and above 100 degrees F)

INACTIVE INGREDIENT

Inactive Ingredients purified water, disodium PEG-12 diemthicone sulfonsuccinate, magnesium aluminum silicate,
glyceryl stearate, tridecyl stearate, neopentyl glycol dicaprylate/dicaprate, tridecyl trimellate, PEG-100 stearate, sorbitol,
dimethyl isosorbide, polyethylene, cetyl esters, anthemis nobilis flower extract, xanthan gum, proplyene glycol, imidazolidinyl urea,
solium hyaluronate, sodium PCA, methylparaben, propylparaben, fragrance